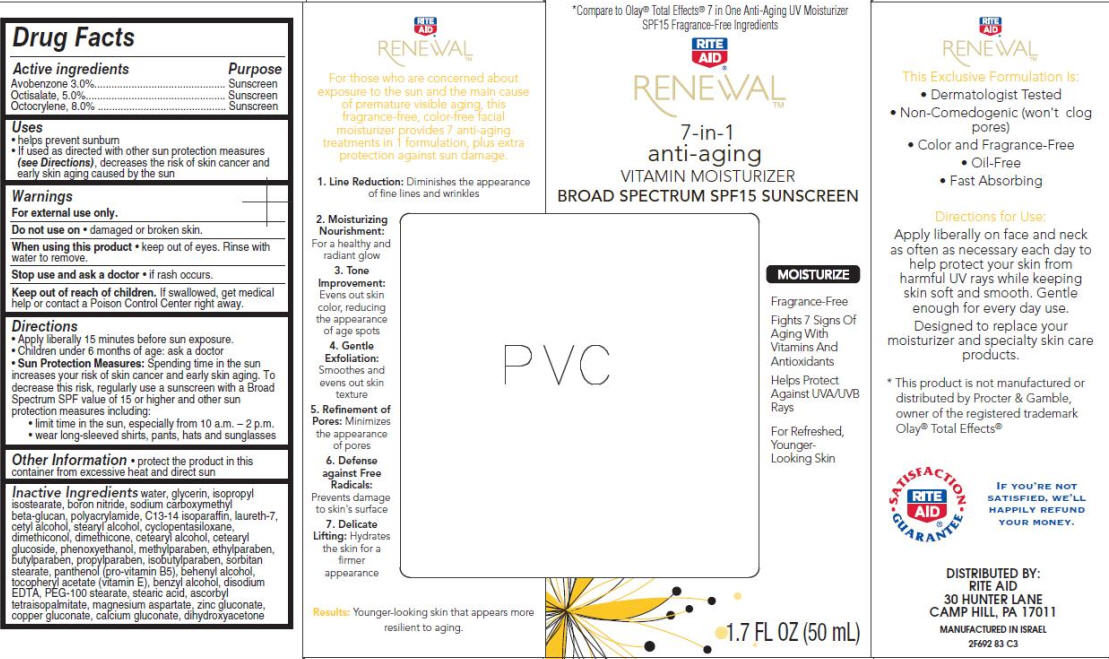 DRUG LABEL: Renewal 7-in-1 Anti-Aging Vitamin
NDC: 11822-3207 | Form: CREAM
Manufacturer: Rite Aid Corporation
Category: otc | Type: HUMAN OTC DRUG LABEL
Date: 20120517

ACTIVE INGREDIENTS: AVOBENZONE 3 mL/100 mL; OCTISALATE 5 mL/100 mL; OCTOCRYLENE 8 mL/100 mL
INACTIVE INGREDIENTS: WATER; GLYCERIN; ISOPROPYL ISOSTEARATE; BORON NITRIDE; SODIUM STARCH GLYCOLATE TYPE A POTATO; C13-14 ISOPARAFFIN; LAURETH-7; CETYL ALCOHOL; STEARYL ALCOHOL; CYCLOMETHICONE 5; DIMETHICONOL (250000 MW); DIMETHICONE; CETOSTEARYL ALCOHOL; CETEARYL GLUCOSIDE; PHENOXYETHANOL; METHYLPARABEN; ETHYLPARABEN; BUTYLPARABEN; PROPYLPARABEN; ISOBUTYLPARABEN; SORBITAN MONOSTEARATE; PANTHENOL; DOCOSANOL; .ALPHA.-TOCOPHEROL ACETATE; BENZYL ALCOHOL; EDETATE DISODIUM; PEG-100 STEARATE; STEARIC ACID; ASCORBYL PALMITATE; MAGNESIUM ASPARTATE; ZINC GLUCONATE; COPPER GLUCONATE; CALCIUM GLUCONATE; DIHYDROXYACETONE; POLYACRYLAMIDE (10000 MW)

Renewal™ 7-in-1 anti-aging VITAMIN MOISTURIZER BROAD SPECTRUM SPF15 SUNSCREEN

Active ingredient

Avobenzone 3.0%

Octisalate 5.0%

Octocrylene 8.0%

Purpose

Sunscreen

Uses

- helps prevent sunburn
- If used as directed with other sun protection measures (see Directions), decreases the risk of skin cancer and early skin aging caused by the sun

Warnings

For external use only.

Do not use on

- damaged or broken skin.

When using this product

- keep out of eyes. Rinse with water to remove.

Stop use and ask a doctor

- if rash occurs.

Keep Out of Reach of Children.

If swallowed, get medical help or contact a Poison Control Center right away.

Directions

- Apply liberally 15 minutes before sun exposure.
- Children under 6 months of age: ask a doctor
- Sun Protection Measures: Spending time in the sun increases your risk of skin cancer and early skin aging. To decrease this risk, regularly use a sunscreen with a Broad Spectrum SPF value of 15 or higher and other sun protection measures including:
  - limit time in the sun, especially from 10 a.m. - 2 p.m.
  - wear long-sleeved shirts, pants, hats and sunglasses

Other Information

- protect the product in this container from excessive heat and direct sun

Inactive Ingredients

water, glycerin, isopropyl isostearate, boron nitride, sodium carboxymethyl beta-glucan, polyacrylamide, C13-14 isoparafﬁn, laureth-7, cetyl alcohol, stearyl alcohol, cyclopentasiloxane, dimethiconol, dimethicone, cetearyl alcohol, cetearyl glucoside, phenoxyethanol, methylparaben, ethylparaben, butylparaben, propylparaben, isobutylparaben, sorbitan stearate, panthenol (pro-vitamin B5), behenyl alcohol, tocopheryl acetate (vitamin E), benzyl alcohol, disodium EDTA, PEG-100 stearate, stearic acid, ascorbyl tetraisopalmitate, magnesium aspartate, zinc gluconate, copper gluconate, calcium gluconate, dihydroxyacetone

Package/Label Principal Display Panel

Rite Aid® RENEWALTM 7-in-1 anti-aging VITAMIN MOISTURIZER BROAD SPECTRUM SPF15 SUNSCREEN

MOISTURIZE

Fragrance-Free

Fights 7 Signs Of Aging With Vitamins And Antioxidants

Helps Protect Against UVA/UVB Rays

For Refreshed, Younger-Looking Skin

1.7 FL OZ (50 mL)

*Compare to Olay® Total Effects® 7 in One Anti-Aging UV Moisturizer
SPF 15 Fragrance-Free Ingredients

DISTRIBUTED BY:
RITE AID
30 HUNTER LANE
CAMP HILL, PA 17011
Manufactured in Israel
2F692 83 C3

Carton Label